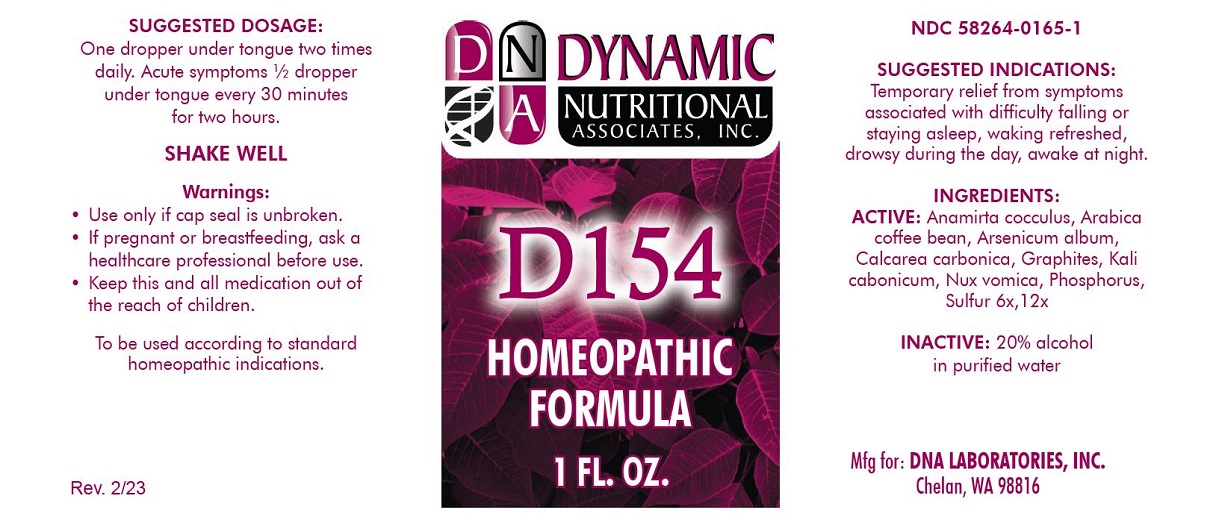 DRUG LABEL: D-154
NDC: 58264-0165 | Form: SOLUTION
Manufacturer: DNA Labs
Category: homeopathic | Type: HUMAN OTC DRUG LABEL
Date: 20250113

ACTIVE INGREDIENTS: OYSTER SHELL CALCIUM CARBONATE, CRUDE 12 [hp_X]/1 mL; SULFUR 12 [hp_X]/1 mL; ARABICA COFFEE BEAN 12 [hp_X]/1 mL; ARSENIC TRIOXIDE 12 [hp_X]/1 mL; GRAPHITE 12 [hp_X]/1 mL; STRYCHNOS NUX-VOMICA SEED 12 [hp_X]/1 mL; ANAMIRTA COCCULUS SEED 12 [hp_X]/1 mL; POTASSIUM CARBONATE 12 [hp_X]/1 mL; PHOSPHORUS 12 [hp_X]/1 mL
INACTIVE INGREDIENTS: ALCOHOL; WATER

D-154

NDC 58264-0165-1

INDICATIONS AND USAGE

PURPOSE

Temporary relief from symptoms associated with difficulty falling asleep or staying asleep, waking refreshed, drowsy during the day, awake at night.

INGREDIENTS

ACTIVE

Anamirta cocculus, Arabica coffee bean, Arsenicum album, Calcarea carbonica, Graphites, Kali carbonicum, Nux vomica, Phosphorus, Sulfur 6x,12x

INACTIVE

20% alcohol in purified water.

SUGGESTED DOSAGE

One dropper under tongue two times daily. Acute symptoms ½ dropper under tongue every 30 minutes for two hours.

STORAGE AND HANDLING

SHAKE WELL

WARNINGS

- Use only if cap seal is unbroken.

PREGNANCY OR BREAST FEEDING

- If pregnant or breastfeeding, ask a health care professional before use.

KEEP OUT OF REACH OF CHILDREN

- Keep this and all medication out of reach of children.

To be used according to standard homeopathic indications.

PRINCIPAL DISPLAY PANEL - 1 FL. OZ. Bottle Label

DYNAMIC

NUTRITIONAL

ASSOCIATES, INC.

D-154

HOMEOPATHIC

1 FL. OZ.